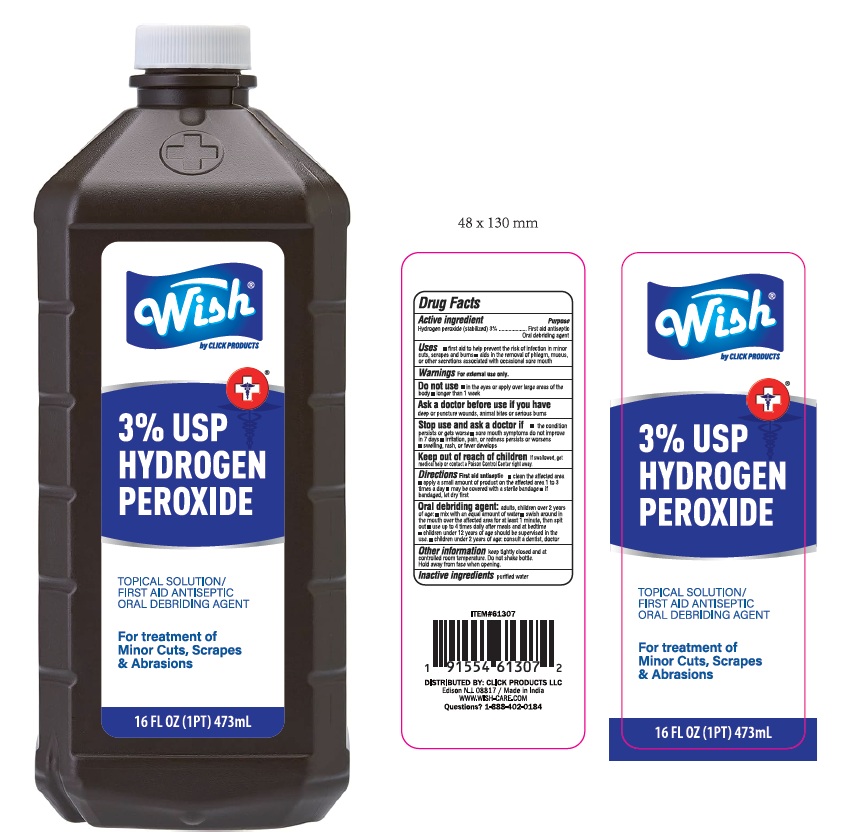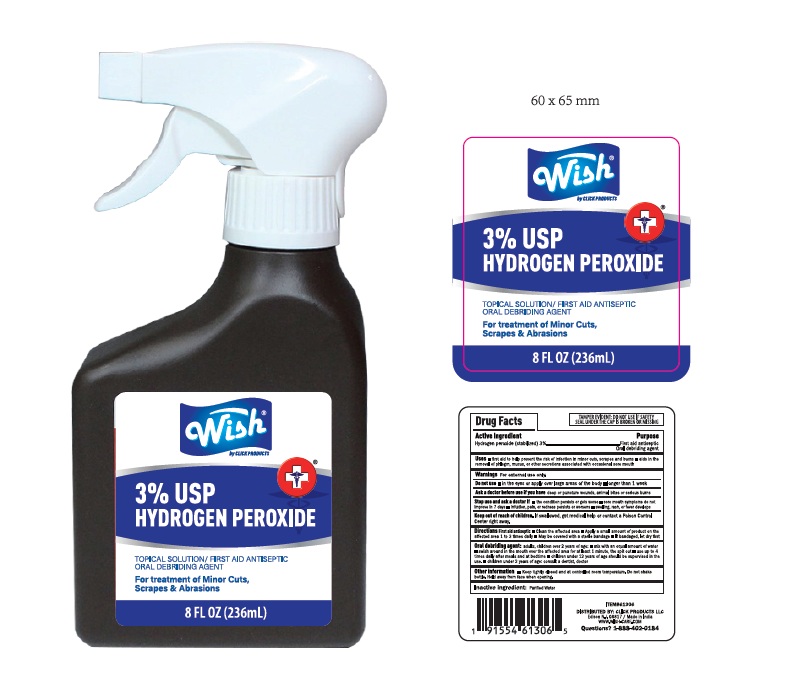 DRUG LABEL: 3% HYDROGEN PEROXIDE
NDC: 84809-005 | Form: LIQUID
Manufacturer: LJ Pharma
Category: otc | Type: HUMAN OTC DRUG LABEL
Date: 20250805

ACTIVE INGREDIENTS: HYDROGEN PEROXIDE 3 mL/100 mL
INACTIVE INGREDIENTS: WATER

Active Ingredient

Hydrogen Peroxide (Stabilized) 3%

Purpose

FIRST AID ANTISEPTIC ORAL DEBRIDING AGENT

Uses

First aid to help prevent the risk of infection in minor cuts, Scrapes & Burns. Aids in the removal of phlegm , mucus or other secretions associated with occasional sore mouth

Warnings

- For external use only
- IF taken internally, Serious gastric disturbances will result. Flammable , Keep away from fire or flame.
- Use only in a well-ventilated area:Fumes may be toxic.

Ask a doctor before use if you havedeep or puncture wounds, Animal bites or serious burns.

When using this product:

- Do not Apply over large areas of the body.
- Do not use longer than one week unless directed by doctor

Stop use and ask doctor ifconditions persist or get worse

Keep out of reach of children In case of ingestion , get medical help or contact a poison. control center right away.

Directions

- Clean the affected Area
- Apply Small amount of this product on the area 1-3 times daily
- Let the alcohol dry on skin before using bandages.
- May be covered with a sterile bandag.

Other information

- Store ate room temperature
- Do not shake bottle Hold away from face when opening.
- Does not contain, nor is intended as a substitute for grain or ethyl alchol.

Inactive Ingredients

Purified Water